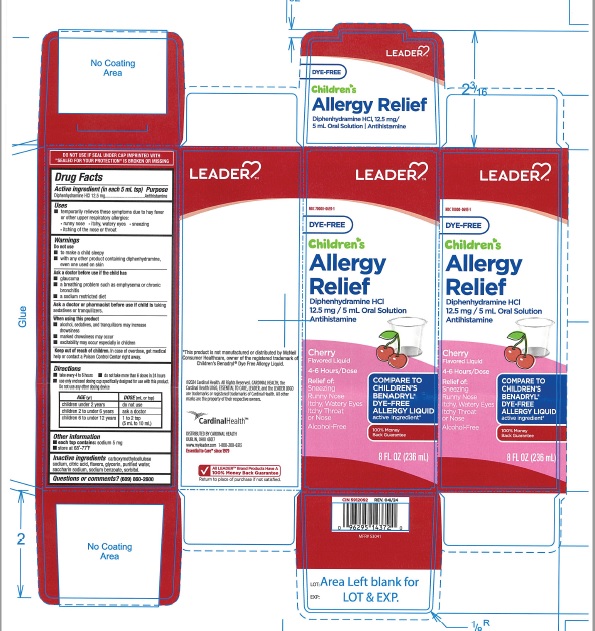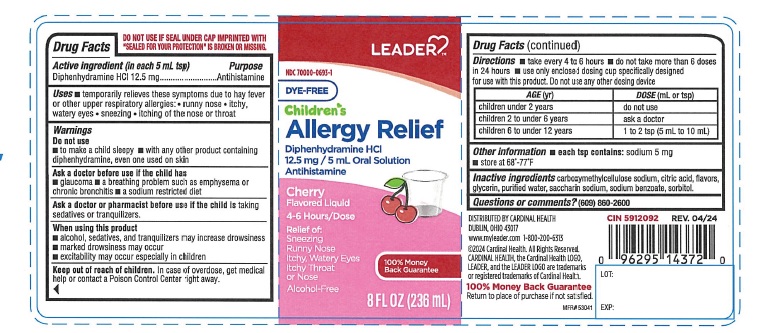 DRUG LABEL: Childrens Allergy Relief Dye Free
NDC: 70000-0693 | Form: LIQUID
Manufacturer: CARDINAL HEALTH 110, LLC. DBA LEADER
Category: otc | Type: Human OTC Drug Label
Date: 20241021

ACTIVE INGREDIENTS: DIPHENHYDRAMINE HYDROCHLORIDE 12.5 mg/5 mL
INACTIVE INGREDIENTS: CARBOXYMETHYLCELLULOSE SODIUM; ANHYDROUS CITRIC ACID; GLYCERIN; WATER; SACCHARIN SODIUM ANHYDROUS; SODIUM BENZOATE; SORBITOL

Leader Childrens Allergy Relief dye free

ACTIVE INGREDIENT(S)

Diphenhydramine HCl 12.5 mg

PURPOSE

Antihistamine

USE(S)

- temporarily relieves these symptoms due to hay fever or other upper respiratory allergies :
- runny nose
- itchy, watery eyes
- sneezing
- itching of the nose or throat

WARNINGS

.

DO NOT USE

- to make a child sleepy
- with any other product containing diphenhydramine, even one used on skin

ASK A DOCTOR BEFORE USE IF THE CHILD HAS

- glaucoma
- a breathing problem such as emphysema or chronic bronchitis
- a sodium restricted diet

ASK A DOCTOR OR PHARMACIST BEFORE USE IF THE CHILD IS

taking sedatives or tranquilizers.

WHEN USING THIS PRODUCT

- alcohol, sedatives, and tranquilizers may increase drowsiness
- marked drowsiness may occur
- excitability may occur especially in children

KEEP OUT OF REACH OF CHILDREN.

In case of overdose, get medical help or contact a Poison Control Center right away.

DIRECTIONS

- take every 4 to 6 hours
- do not take more than 6 doses in 24 hours
- use only enclosed dosing cup specifically designed for use with this product. Do not use any other dosing device

AGE(yr) | DOSE(mL or tsp)
children under 2 years | do not use
children 2 to under 6 years | ask a doctor
children 6 to under 12 years | 1 to 2 tsp (5 mL to 10 mL)

OTHER INFORMATION

- each tsp contains: sodium 5 mg
- store at 68o -77o F

INACTIVE INGRADIENTS

carboxymethylcellulose sodium, citric acid, flavors, glycerin, purified water, saccharin sodium, sodium benzoate, sorbitol.

QUESTIONS OR COMMENTS?

(609) 860-2600

PRINCIPAL DISPLAY PANEL

NDC 70000-0693-1

DYE-FREE

Children's Allergy Relief

Diphenhydramine HCl

12.5mg /5 mL Oral Solution

Antihistamine

Cherry

Flavored Liquid

4-6 hours/Dose

Relief of:

Sneezing

Runny Nose

itchy, water eyes

itchy Throat

or Nose

Alcohol -Free

100% Money Back Guarantee

8 FL OZ (236 mL)